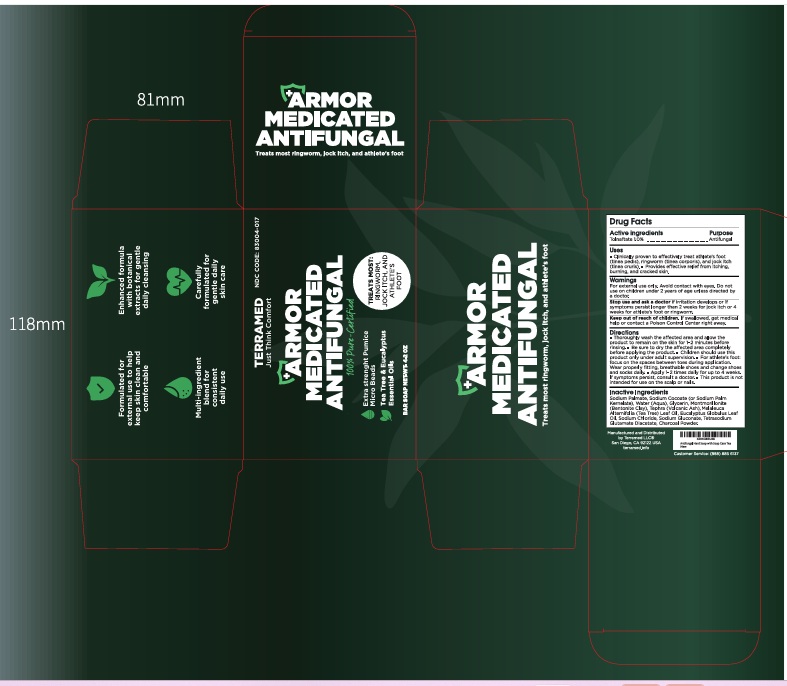 DRUG LABEL: Terramed Just Think Comfort Armor Antifungal Medicated
NDC: 83004-017 | Form: SOAP
Manufacturer: Rida LLC
Category: otc | Type: HUMAN OTC DRUG LABEL
Date: 20260204

ACTIVE INGREDIENTS: TOLNAFTATE 1 g/100 g
INACTIVE INGREDIENTS: SODIUM PALMATE; SODIUM COCOATE; WATER; GLYCERIN; MELALEUCA ALTERNIFOLIA LEAF; EUCALYPTUS OIL; SODIUM CHLORIDE; SODIUM GLUCONATE; TETRASODIUM GLUTAMATE DIACETATE; ACTIVATED CHARCOAL

Active Ingredient

Tolnaftate 1%

Purpose

Antifungal

Uses

● Proven clinically effective in the treatment of most athlete's foot (tinea pedis), ringworm (tinea corporis) and jock itch (tinea cruris).
● For effective relief of itching, burning and cracking skin.

Warnings

For external use only
When using this productavoid contact with the eye

Stop use and ask a doctor ifirritation occurs or if there is no improvement within 2 weeks for jock itch or within 4 weeks for athlete's foot and ringworm.

Do Not use onchildren under 2 under of age except under the advice and supervision of a doctor.

Keep out of reach of children. If swallowed, get medical help or contact a Poison Control Center right away.

Directions

● Wash affected area well and let product sit 1-2 minutes before rinsing.
● Make sure to dry affected area thoroughly.
● Supervise children in the use of this product.
● For Athlete's foot: pay special attention to the spaces between the toes; wear well-fitting, ventilated shoes and change shoes and socks at least once daily.
● Use 1-2 times daily. Use daily for 4 weeks; if condition persists longer, ask a doctor.
● This product is not effective on the scalp or nails.

Inactive ingredients

Sodium Palmate, Sodium Palm Kernelate, Water, Glycerin, Sodium Gluconate, Eucalyptus Globulus Leaf Oil, Melaleuca Alternifolia (Tea Tree) Leaf Oil, Palm Acid, Sodium Chloride, Palm Kernel Acid, Charcoal Powder